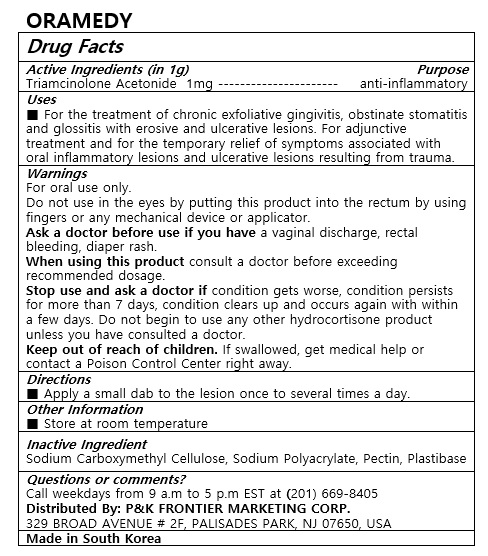 DRUG LABEL: ORAMEDY
NDC: 72689-0039 | Form: OINTMENT
Manufacturer: OASIS TRADING
Category: otc | Type: HUMAN OTC DRUG LABEL
Date: 20190319

ACTIVE INGREDIENTS: TRIAMCINOLONE ACETONIDE 1 mg/1 g
INACTIVE INGREDIENTS: SODIUM POLYACRYLATE (2500000 MW); PECTIN; CARBOXYMETHYLCELLULOSE SODIUM

ACTIVE INGREDIENT

Triamcinolone Acetonide

PURPOSE

For the treatment of chronic exfoliative gingivitis, obstinate stomatitis and glossitis with erosive and ulcerative lesions. For adjunctive treatment and for the temporary relief of symptoms associated with oral inflammatory lesions and ulcerative lesions resulting from trauma.

Keep out of reach of children

INDICATIONS AND USAGE

Apply a small dab to the lesion once to several times a day.

WARNINGS

For external use only.

Do not use in the eyes by putting this product into the rectum by using fingers or any mechanical device or applicator.

Ask a doctor before use if you have a vaginal discharge, rectal bleeding, diaper rash.

When using this product consult a doctor before exceeding recommended dosage.

Stop use and ask a doctor if condition gets worse, condition persists for more than 7 days, condition clears up and occurs again with within a few days. Do not begin to use any other hydrocortisone product unless you have consulted a doctor.

Keep out of reach of children. If swallowed, get medical help or contact a Poison Control Center right away.

INACTIVE INGREDIENT

Sodium Carboxymethyl Cellulose, Sodium Polyacrylate, Pectin, Plastibase

DOSAGE AND ADMINISTRATION

For buccal use only